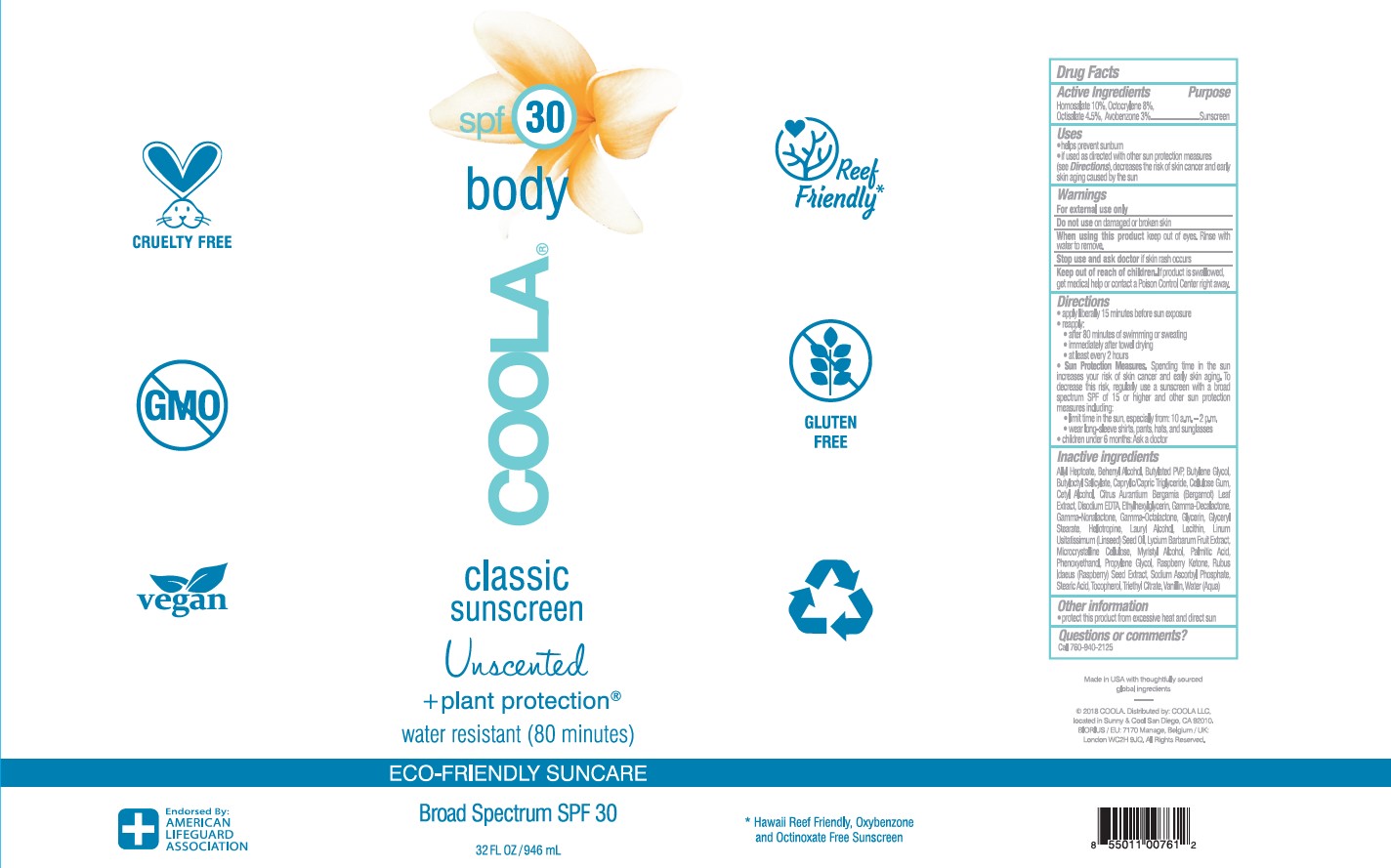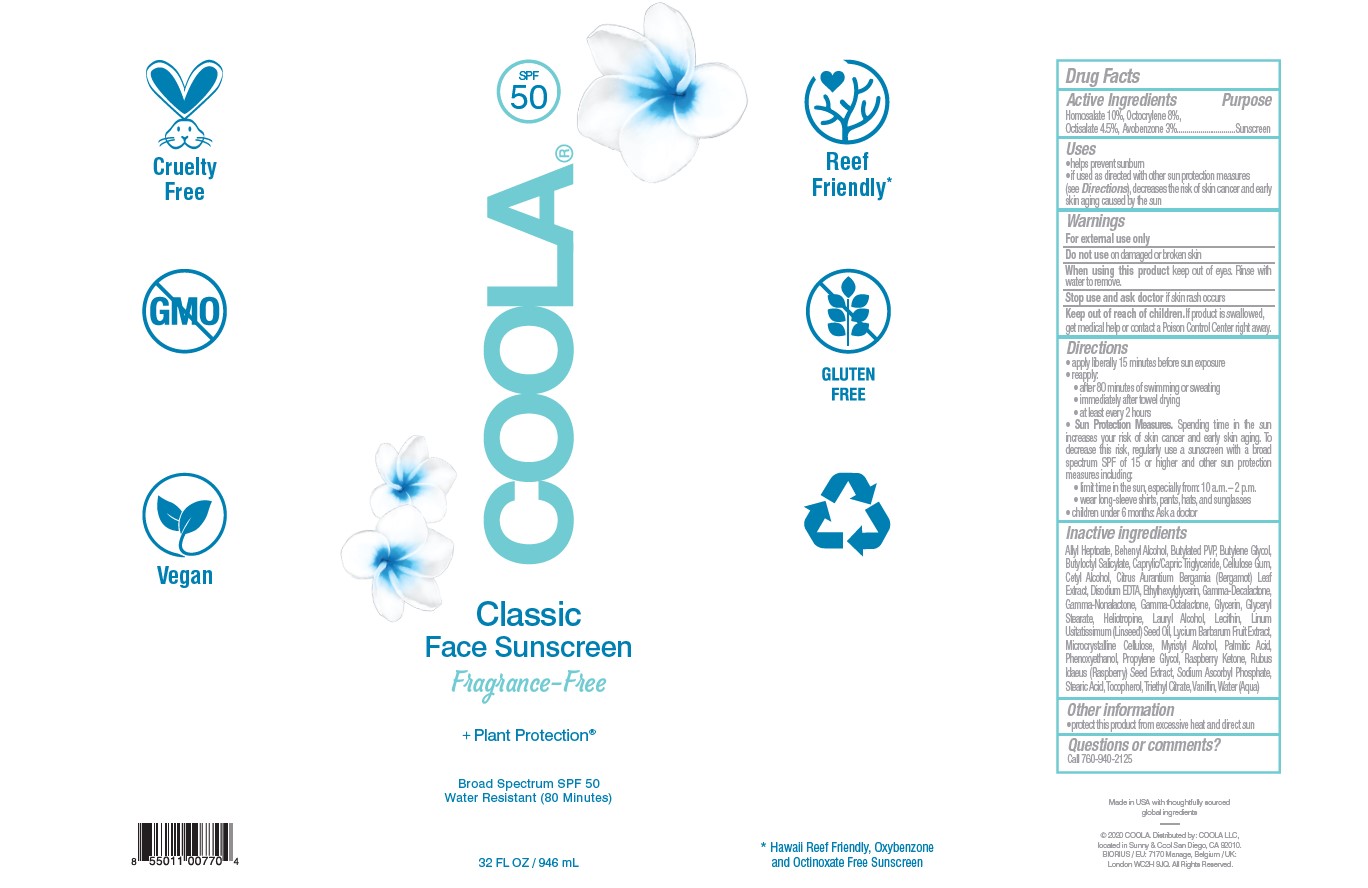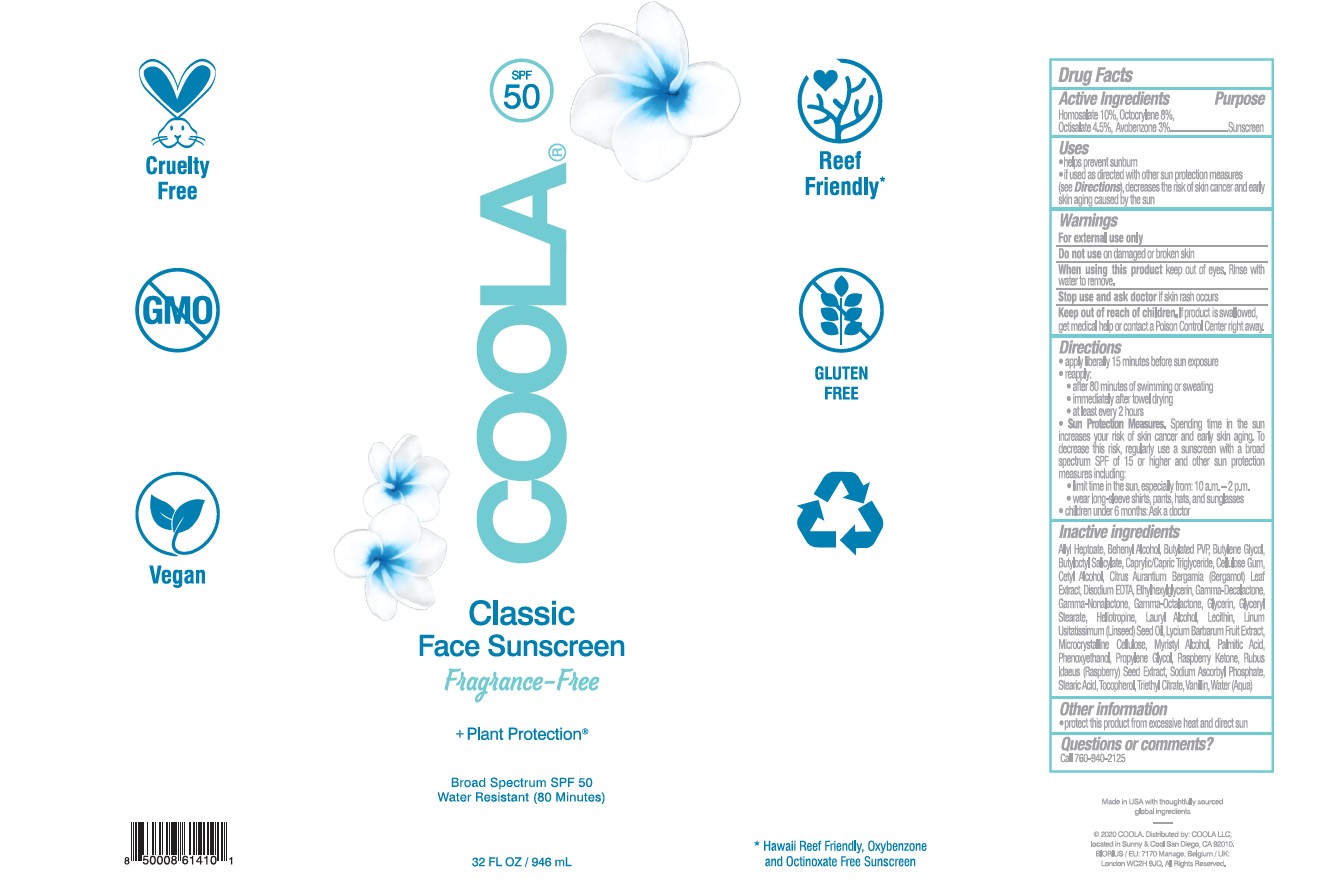 DRUG LABEL: COOLA CLASSIC SUNSCREEN FRAGRANCE FREE
NDC: 79753-045 | Form: LOTION
Manufacturer: COOLA, LLC
Category: otc | Type: HUMAN OTC DRUG LABEL
Date: 20251214

ACTIVE INGREDIENTS: HOMOSALATE 100 mg/1 mL; AVOBENZONE 30 mg/1 mL; OCTOCRYLENE 80 mg/1 mL; OCTISALATE 45 mg/1 mL
INACTIVE INGREDIENTS: WATER; CETYL ALCOHOL; RASPBERRY SEED OIL; GLYCERYL 1-STEARATE; .ALPHA.-TOCOPHEROL, DL-; GLYCERIN; BUTYLOCTYL SALICYLATE; MEDIUM-CHAIN TRIGLYCERIDES; ETHYLHEXYLGLYCERIN; PHENOXYETHANOL; LYCIUM BARBARUM FRUIT; MONARDA DIDYMA LEAF; .GAMMA.-NONALACTONE; .GAMMA.-DECALACTONE; SODIUM ASCORBYL PHOSPHATE; ALLYL HEPTANOATE; 4-(P-HYDROXYPHENYL)-2-BUTANONE; STEARIC ACID; PALMITIC ACID; LAURYL ALCOHOL; EDETATE DISODIUM; PIPERONAL; MYRISTYL ALCOHOL; PROPYLENE GLYCOL; CARBOXYMETHYLCELLULOSE SODIUM (0.7 CARBOXYMETHYL SUBSTITUTION PER SACCHARIDE; 1200 MPA.S AT 1%); LECITHIN, SOYBEAN; DOCOSANOL; VANILLIN; TRIETHYL CITRATE; CELLULOSE, MICROCRYSTALLINE; BUTYLENE GLYCOL; LINSEED OIL; .GAMMA.-OCTALACTONE

COOLA CLASSIC SUNSCREEN LOTION FRAGRANCE-FREE

Active ingredients

Avobenzone 3.0%

Homosalate 10.0%

Octisalate 4.5%

Octocrylene 8.0%

Purpose

Sunscreen

Uses

- helps prevent sunburn
- if used as directed with other sun protection measures (see Directions), decreases the risk of skin cancer and early skin aging caused by the sun

Warnings

For external use only

Do not use

- on damaged or broken skin.

When using this product

- keep out of eyes. Rinse with water to remove.

Stop use and ask a doctor if

- rash occurs.

Keep out of the reach of children

If swallowed, get medical help or contact a Poison Control Center right away.

Directions

- apply liberally 15 minutes before sun exposure

- reapply:

-after 80 minutes of swimming or sweating

-immediately after towel drying

-at least every 2 hours

- children under 6 months of age: ask a doctor
- Sun Protection Measures. Spending time in the sun increases your risk of skin cancer and early skin aging. To decrease this risk, regularly use a sunscreen with a Broad Spectrum SPF value of 15 or higher and other sun protection measures including:

-limit time in the sun, especially from 10 a.m.-2 p.m.

-wear long-sleeved shirts, pants, hats, and sunglasses

Other information

- protect this product from excessive heat and direct sun
- may stain or damage some fabrics, materials or surfaces

Inactive Ingredients

Alkyl Heptoate, Behenyl Alcohol, Butylated PVP, Butylene Glycol, Butyloctyl Salicylate, Caprylic/Capric Triglyceride, Cellulose Gum, Cetyl Alcohol, Citrus Aurantium Bergamia (Bergamot) Leaf Extract, Disodium EDTA, Ethylhexylglycerin, Gamma-Decalactone, Gamma-Nonalactone, Glycerin, Glyceryl Stearate, Heliotropine, Lauryl Alcohol, Lecithin, Linum Usitatissimum (Linseed) Seed Oil, Lycium Barbarum Fruit Extract, Microcrystalline Cellulose, Myristyl Alcohol, Palmitic Acid, Phenoxyethanol, Propylene Glycol, Raspberry Ketone, Rubus Idaeus (Raspberry) Seed Extract, Sodium Ascorbyl Phosphate, Stearic Acid, Tocopherol, Triethyl Citrate, Vanillin, Water (Aqua)